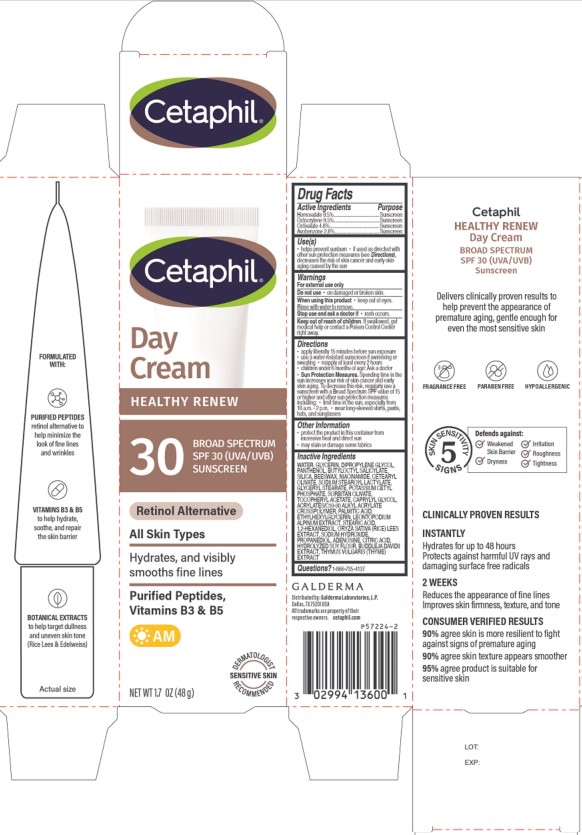 DRUG LABEL: Cetaphil Healthy Renew Day Cream Broad Spectrum SPF 30
NDC: 0299-4136 | Form: LOTION
Manufacturer: Galderma Laboratories, L.P.
Category: otc | Type: HUMAN OTC DRUG LABEL
Date: 20250127

ACTIVE INGREDIENTS: Homosalate 95 mg/1 g; Octocrylene 95 mg/1 g; Octisalate 48 mg/1 g; Avobenzone 28 mg/1 g
INACTIVE INGREDIENTS: Water; Glycerin; Dipropylene Glycol; Panthenol; Butyloctyl Salicylate; Silicon Dioxide; Yellow Wax; Niacinamide; Cetearyl Olivate; Sodium Stearoyl Lactylate; Glyceryl Monostearate; Potassium Cetyl Phosphate; Sorbitan Olivate; .Alpha.-Tocopherol Acetate; Caprylyl Glycol; Carbomer Interpolymer Type A (Allyl Sucrose Crosslinked); Palmitic Acid; Ethylhexylglycerin; Leontopodium Nivale Subsp. Alpinum Root; Stearic Acid; 1,2-Hexanediol; Rice Germ; Sodium Hydroxide; Propanediol; Adenosine; Citric Acid Monohydrate; Hydrolyzed Soy Protein (Enzymatic; 2000 Mw); Buddleja Davidii Whole; Thyme

Drug Facts

Active Ingredients.....Purpose

Homosalate 9.5% .................Sunscreen
Octocrylene 9.5% .........… Sunscreen
Octisalate 4.8% ...............… Sunscreen
Avobenzone 2.8% ................. Sunscreen

Purpose

Sunscreen

Uses

- helps prevent sunburn
- if used as directed with other sun protection measures (see Directions), decreases the risk of skin cancer and early skin aging caused by the sun

Warnings

For external use only

Do not use

▪ on damaged or broken skin

When using this product

• keep out of eyes. Rinse with water to remove.

Stop use and ask a doctor if

• rash occurs.

Keep out of reach of children.

If swallowed, get medical help or contact a Poison Control Center right away.

Directions

- apply liberally 15 minutes before sun exposure
- use a water resistant sunscreen if swimming or sweating
- reapply at least every 2 hours
- children under 6 months of age: Ask a doctor
- Sun Protection Measures. Spending time in the sun increases your risk of skin cancer and early skin aging. To decrease this risk, regularly use a sunscreen with a Broad Spectrum SPF value of 15 or higher and other sun protection measures including:
- limit time in the sun, especially from 10 a.m. - 2 p.m.
- wear long-sleeved shirts, pants, hats, and sunglasses

Other information

- protect the product in this container from excessive heat and direct sun
- may stain or damage some fabrics

Inactive Ingredients

WATER, GLYCERIN, DIPROPYLENE GLYCOL, PANTHENOL, BUTYLOCTYL SALICYLATE, SILICA, BEESWAX, NIACINAMIDE, CETEARYL OLIVATE, SODIUM STEAROYL LACTYLATE, GLYCERYL STEARATE, POTASSIUM CETYL PHOSPHATE, SORBITAN OLIVATE, TOCOPHERYL ACETATE, CAPRYLYL GLYCOL, ACRYLATES/C10-30 ALKYL ACRYLATE CROSSPOLYMER, PALMITIC ACID, ETHYLHEXYLGLYCERIN, LEONTOPODIUM ALPINUM EXTRACT, STEARIC ACID, 1,2-HEXANEDIOL, ORYZA SATIVA (RICE) LEES EXTRACT, SODIUM HYDROXIDE, PROPANEDIOL, ADENOSINE, CITRIC ACID, HYDROLYZED SOY FLOUR, BUDDLEJA DAVIDII EXTRACT, THYMUS VULGARIS (THYME) EXTRACT

Questions or comments?

1-866-735-4137

Principal Display Panel - 1.7 OZ Carton

Cetaphil®
DAY
CREAM
HEALTHY RENEW

30
BROAD SPECTRUM
SPF 30 (UVA/UVB)
SUNSCREEN
Retinol Alternative
All Skin Types
Hydrates, and visibly
smooths fine lines
Purified Peptides,
Vitamins B3 & B5
Dermatologist Recommended Sensitive Skin Icon
NET WT 1.7 OZ (48 g)

Distributed by:
Galderma Laboratories, L.P., Dallas, TX 75201 USA
All trademarks are the property of their respective owners.
cetaphil.com
P57224-2